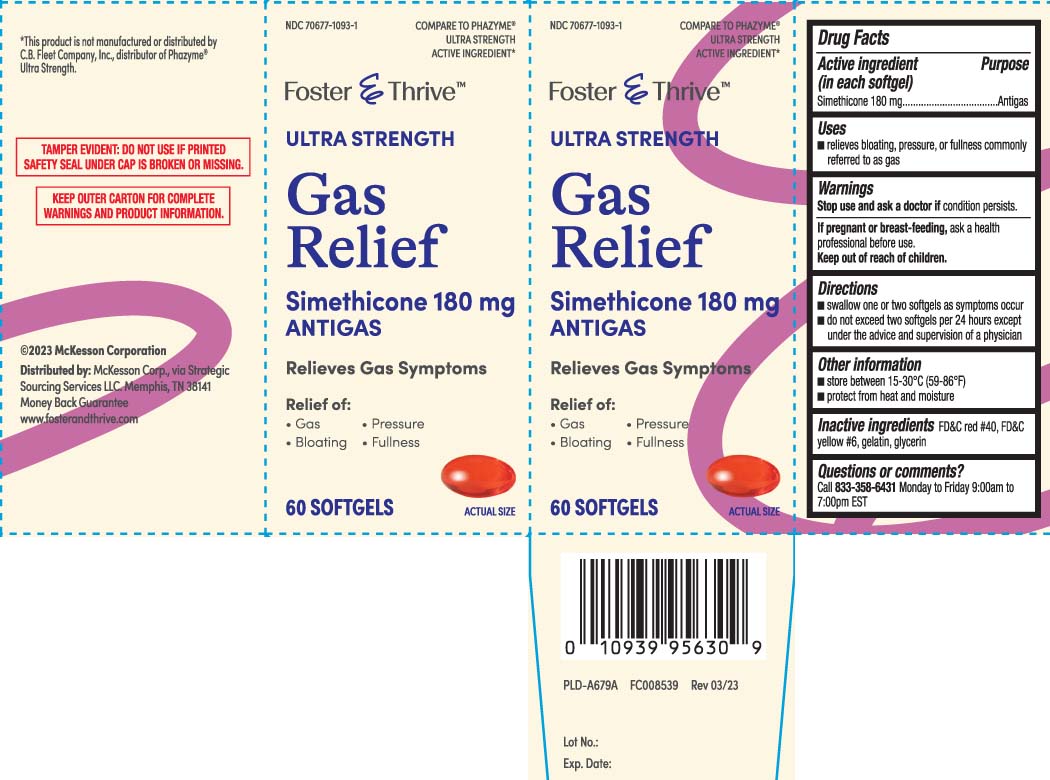 DRUG LABEL: Gas Relief
NDC: 70677-1093 | Form: CAPSULE, LIQUID FILLED
Manufacturer: Strategic Sourcing Services LLC
Category: otc | Type: HUMAN OTC DRUG LABEL
Date: 20240531

ACTIVE INGREDIENTS: DIMETHICONE 180 mg/1 1
INACTIVE INGREDIENTS: FD&C YELLOW NO. 6; GELATIN; GLYCERIN; FD&C RED NO. 40

Drug Facts

Active ingredient (in each softgel)

Simethicone 180 mg

Purpose

Antigas

Uses

- relieves bloating, pressure, or fullness commonly referred to as gas

Warnings

Stop use and ask a doctor if

condition persists.

If pregnant or breast-feeding,

ask a health professional before use.

Directions

- swallow one or two softgels as symptoms occur
- do not exceed two softgels per 24 hours except under the advice and supervision of a physician

Other information

- store between 15-30ºC (59-86ºF)
- protect from heat and moisture

Inactive ingredients

FD&C red #40 FD&C yellow #6, gelatin, glycerin

Questions or comments?

Call 1-833-358-6431 Monday to Friday 9:00am to 7:00pm EST

Principal Display Panel

COMPARE TO PHAZYME® ULTRA STRENGTH ACTIVE INGREDIENT*

ULTRA STRENGTH

Gas Relief

Simethicone 180 mg

ANTIGAS

Relieves Gas Symptoms

Relief of:

- Gas
- Pressure
- Bloating
- Fullness

SOFTGELS

*This product is not manufactured or distributed by C.B. Fleet Company Inc., distributor of Phazyme® Ultra Strength

TAMPER EVIDENT: DO NOT USE IF PRINTED SAFETY SEAL UNDER CAP IS BROKEN OR MISSING.

KEEP OUTER CARTON FOR COMPLETE WARNINGS AND PRODUCT INFORMATION.

Distributed by McKesson Corp.,

via Strategic Sourcing Services LLC.

Memphic, TN 38141

www.fosterandthrive.com

Product Label

FOSTER & THRIVE Ultra Strength Gas Relief